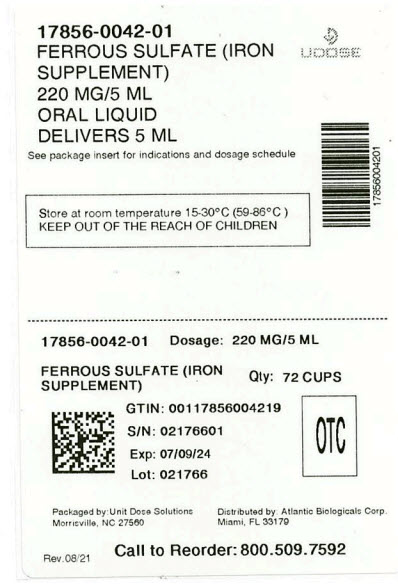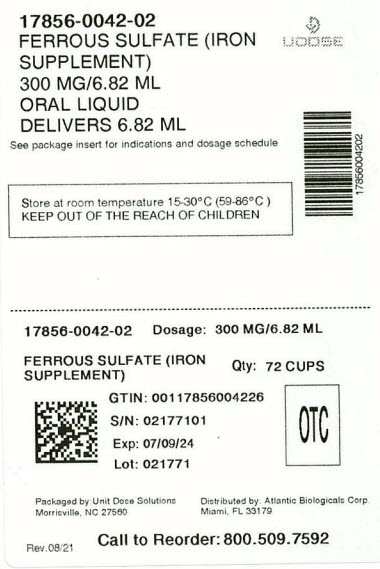 DRUG LABEL: ONE VITE Iron Supplement Liquid
NDC: 17856-0042 | Form: LIQUID
Manufacturer: ATLANTIC BIOLOGICALS CORP
Category: other | Type: DIETARY SUPPLEMENT
Date: 20240129

ACTIVE INGREDIENTS: FERROUS SULFATE 220 mg/5 mL
INACTIVE INGREDIENTS: ANHYDROUS CITRIC ACID; FD&C YELLOW NO. 6; SODIUM BENZOATE; SUCRALOSE; SUCROSE; WATER

ONE-VITE
Ferrous Sulfate
220 mg / 5 mL
Iron Supplement Liquid
For the treatment of iron deficiency and iron deficiency anemia

STATEMENT OF IDENTITY

Supplement Facts
Serving Size: 1 teaspoonful (5 mL) Servings per container: 94
Amount per teaspoonful (5 mL) %Daily Value * | % Daily Value
Calories 4
Total Carbohydrate 1g | <1%
Total Sugars 1g | **
includes 1g Added Sugars | 2%
Iron (elemental) (from ferrous sulfate) 44mg | 244%
*% Daily Value tells you how much a nutrient in a serving of food contributes to a daily diet. 2,000 calories a day is used for general nutrition advice. **Daily Value not established

HEALTH CLAIM

Each teaspoonful (5mL) contains 220mg Ferrous Sulfate, providing approximately 44mg of elemental iron.

OTHER INGREDIENTS: Anhydrous citric acid, Dye FD&C yellow #6, Flavor cherry, Sodium Benzoate, Sucralose, Sucrose, Purified water.

SAFE HANDLING WARNING

WARNING: Accidental overdose of iron containing supplements is a leading cause of fatal poisoning in children under 6.
KEEP THIS PRODUCT OUT OF REACH OF CHILDREN.
In case of accidental overdose, call a doctor or Poison Control Center immediately.

WARNINGS

see boxed warning above.

PRECAUTIONS

CAUTION: Do not exceed suggested serving size.

The treatment of any anemic condition should be under the advice and supervision of a doctor. Since oral iron products interfere with absorption of oral tetracycline antibiotics, these products should not be taken within two (2) hours of each other.
This product may occasionally cause constipation, diarrhea, or may color stool black. It may cause gastrointestinal discomfort (such as nausea) which may be minimized by taking with meals.
As with any supplement, if you are pregnant, nursing, taking medication, or under a doctor's care for any condition, ask a health professional before use.
OTHER INFORMATION: Store at room temperature 15-30°C (59-86°F)

Tamper-Evident: Do not use if foil seal over bottle opening is torn, broken or missing.
Pharmacist: Dispense in a tight, light-resistant container with a child resistant cap as defined in the USP.

DOSAGE AND ADMINISTRATION

SUGGESTED USE: Adults and children 12 years and over, take one (1) teaspoonful daily with or after a meal as a dietary supplement, or as directed by your doctor.
Children under 12, consult a doctor.
Mix with water or juice to avoid temporary staining of teeth. Do not mix with milk or wine-based vehicles.

DISTRIBUTED BY

ATLANTIC BIOLOGICALS CORP

MIAMI, FL 33179